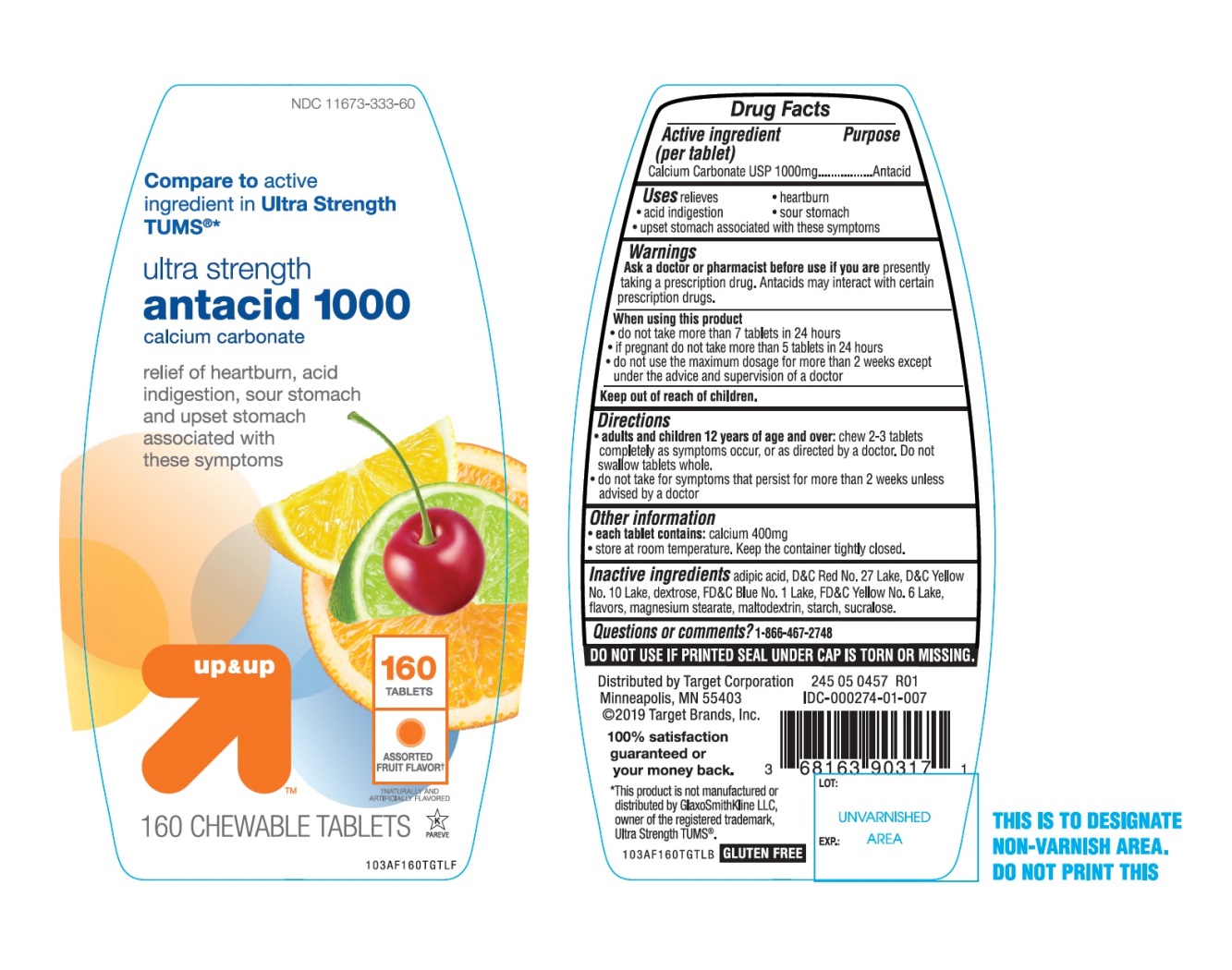 DRUG LABEL: ultra strength

NDC: 11673-333 | Form: TABLET, CHEWABLE
Manufacturer: Target Corporation
Category: otc | Type: HUMAN OTC DRUG LABEL
Date: 20251104

ACTIVE INGREDIENTS: CALCIUM CARBONATE 1000 mg/1 1
INACTIVE INGREDIENTS: ADIPIC ACID; D&C RED NO. 27; D&C YELLOW NO. 10; DEXTROSE, UNSPECIFIED FORM; FD&C BLUE NO. 1; FD&C YELLOW NO. 6; MAGNESIUM STEARATE; MALTODEXTRIN; STARCH, CORN; SUCRALOSE

Ultra strength antacid 1000 chewable tablets

Active ingredient (per tablet)

Calcium Carbonate USP 1000mg

Purpose

Antacid

Uses

relieves

- heartburn
- acid indigestion
- sour stomach
- upset stomach associated with these symptoms

Warnings

Ask a doctor or pharmacist before use if you arepresently taking a prescription drug. Antacids may interact with certain prescription drugs.

When using this product

- do not take more than 7 tablets in 24 hours
- if pregnant do not take more than 5 tablets in 24 hours
- do not use the maximum dosage for more than 2 weeks except under the advice and supervision of a doctor.

Directions

- adults and children 12 years of age and over:chew 2-3 tablets completely as symptoms occur, or as directed by a doctor. Do not swallow tablets whole.
- do not take for symptoms that persist for more than 2 weeks unless advised by a doctor

Other information

- each tablet contains:elemental calcium 400mg
- store at room temperature. Keep the container tightly closed.

Inactive ingredients

adipic acid, D&C Red No. 27 Lake, D&C Yellow No. 10 Lake, dextrose, FD&C Blue No. 1 Lake, FD&C Yellow No. 6 Lake, flavors, magnesium stearate, maltodextrin, starch, sucralose.

Questions?

1-866-467-2748

Package/Label Principal Display Panel

NDC 11673-333-60

Compare to the active ingredient in Ultra Strength Tums®

ULTRA STRENGTH

Antacid Tablets

Calcium Carbonate 1000 mg

Fast Relief of Upset Stomach, Heartburn and Acid Indigestion

Assorted Fruit

Naturally and Artificially Flavored

160 Chewable Tablets

GLUTEN-FREE

Dist. by Target Corp.

Minneapolis, MN 55403

©2019 Target Brands, Inc.

*This product is not manufactured or distributed by GlaxoSmithKline LLC, owner of the registered trademark Ultra Strength Tums®.

GLUTEN FREE

SAFETY SEALED: DO NOT USE IF PRINTED SEAL UNDER CAP IS TORN OR MISSING